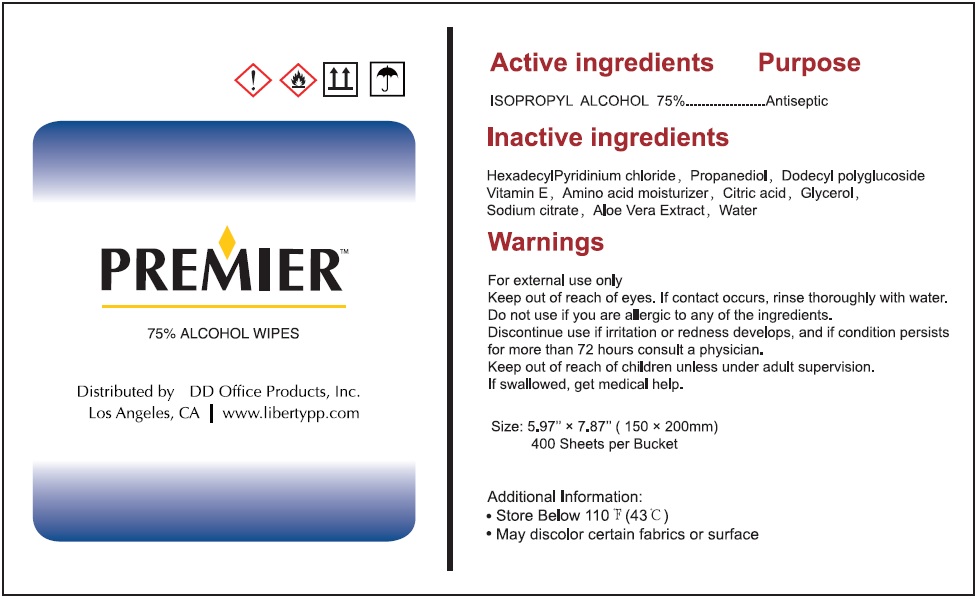 DRUG LABEL: 400 Wet Wipes
NDC: 77081-002 | Form: CLOTH
Manufacturer: D D Office Products, Inc.
Category: otc | Type: HUMAN OTC DRUG LABEL
Date: 20200713

ACTIVE INGREDIENTS: ISOPROPYL ALCOHOL 75 mL/100 mL
INACTIVE INGREDIENTS: CETYLPYRIDINIUM CHLORIDE; PROPANEDIOL; LAURYL GLUCOSIDE; .ALPHA.-TOCOPHEROL; BETAINE; CITRIC ACID MONOHYDRATE; GLYCERIN; SODIUM CITRATE, UNSPECIFIED FORM; ALOE VERA LEAF; WATER

PREMIER ALCOHOL WIPES

Active ingredients

ISOPROPYL ALCOHOL 75%

Purpose

Antiseptic

Use

hand sanitizer to decrease bacteria on the skin.

Warnings

For external use only

Keep out of reach of eyes. If contact occurs, rinse thoroughly with water.

Do not use if you are allergic to any of the ingredients.

Discontinue use if irritation or redness develops, and if condition persists for more than 72 hours consult a physician.

Keep out of reach of children unless under adult supervision.

If swallowed, get medical help.

Direction

Wet hands thoroughly with product and allow to dry without wiping.

Additional Information:

• Store below 110 °F (43°C)

• May discolor certain fabrics or surfaces

Inactive ingredients

HexadecylPyridinium chloride, Propanediol, Dodecyl polyglucoside Vitamin E, Amino acid moisturizer, Citric acid, Glycerol, Sodium citrate, Aloe Vera Extract, Water

75% ALCOHOL WIPES

Distributed by DD Office Products, Inc.

Los Angeles, CA | www.libertypp.com